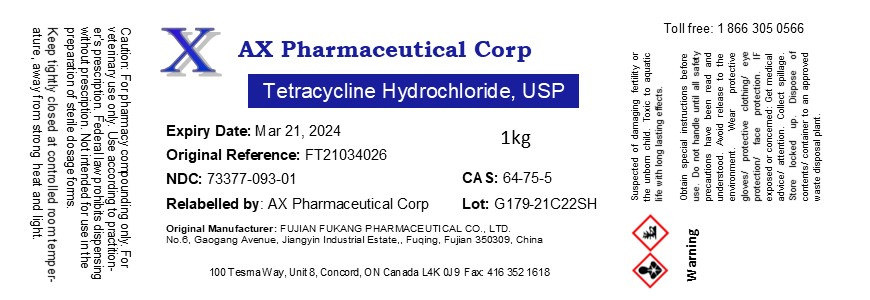 DRUG LABEL: Tetracycline Hydrochloride
NDC: 73377-093 | Form: POWDER
Manufacturer: AX Pharmaceutical Corp
Category: other | Type: BULK INGREDIENT
Date: 20210429

ACTIVE INGREDIENTS: TETRACYCLINE HYDROCHLORIDE 1 kg/1 kg

Tetracycline Hydrochloride